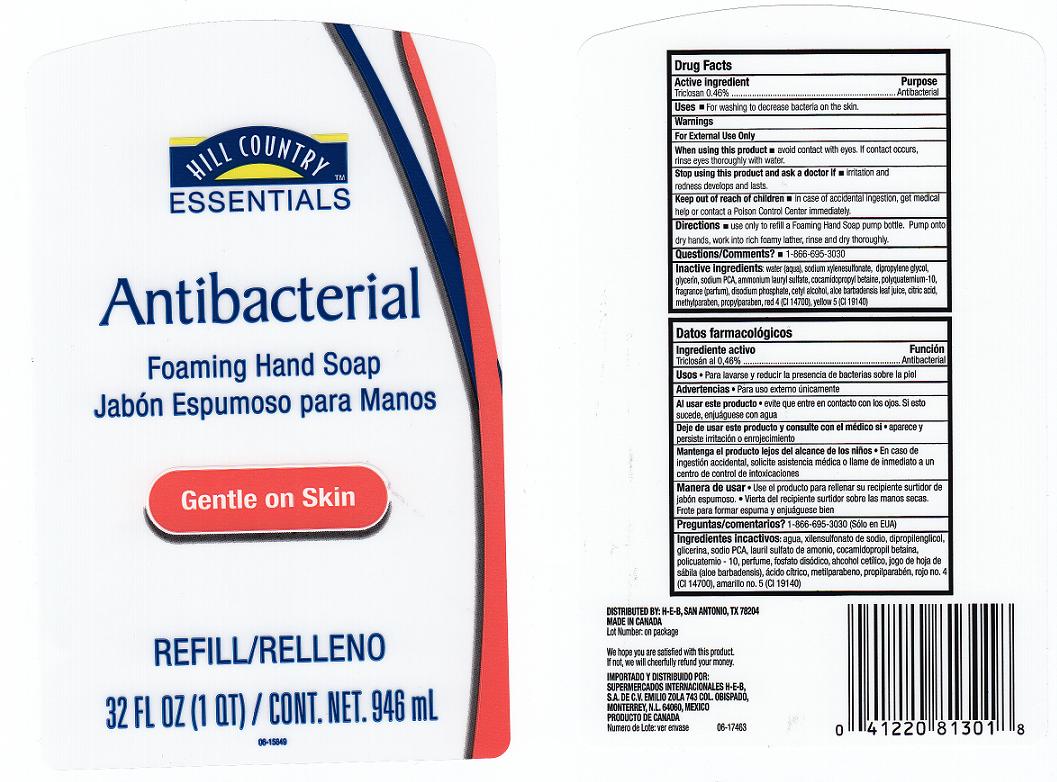 DRUG LABEL: ANTIBACTERIAL FOAMING 
NDC: 37808-177 | Form: LIQUID
Manufacturer: H E B
Category: otc | Type: HUMAN OTC DRUG LABEL
Date: 20111102

ACTIVE INGREDIENTS: TRICLOSAN 0.46 mL/100 mL
INACTIVE INGREDIENTS: WATER; SODIUM  XYLENESULFONATE; DIPROPYLENE GLYCOL; GLYCERIN; SODIUM PYRROLIDONE CARBOXYLATE; AMMONIUM LAURYL SULFATE; COCAMIDOPROPYL BETAINE; POLYQUATERNIUM-10 (400 CPS AT 2%); SODIUM PHOSPHATE, DIBASIC, DIHYDRATE; CETYL ALCOHOL; ALOE VERA LEAF; CITRIC ACID MONOHYDRATE; METHYLPARABEN; PROPYLPARABEN; FD&C RED NO. 4; FD&C YELLOW NO. 5

DRUG FACTS

Active Ingredient

Triclosan 0.46%

Purpose

Antibacterial

Uses

For washing to decrease bacteria on the skin.

Warnings

For external use only.

When using this product

Avoid contact with eyes. If contact occurs, rinse eyes thoroughly with water.

Stop using this product and ask doctor if

Irritation or redness develops and lasts.

Keep out of reach of children

In case of accidental ingestion, get medical help and contact a Poison Control Center immediately.

Directions

Use only to refill a Foaming Hand Soap pump bottle. Pump onto dry hands, work into a lather, rinse and dry thoroughly.

Questions or Comments

1-866-695-3030

Inactive ingredients

Water (Aqua), Sodium Xylenesulfonate, Dipropylene Glycol, Glycerin, Sodium PCA, Ammonium Lauryl Sulfate, Cocamidopropyl Betaine, Polyquaternium-10, Fragrance (Parfum), Disodium Phosphate, Cetyl Alcohol, Aloe Barbadensis Leaf Juice, Citric Acid, Methylparaben, Propylparaben, Red 4 (CI 14700), Yellow 5 (CI 19140).